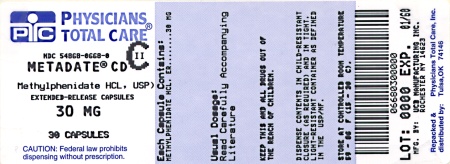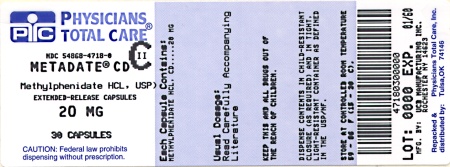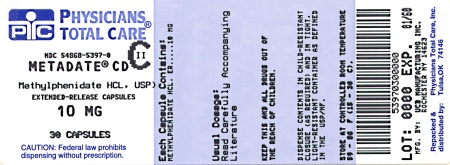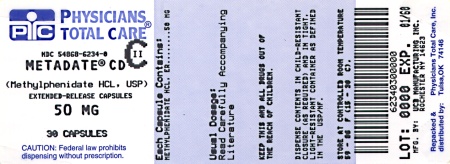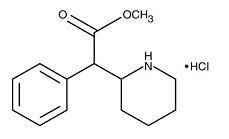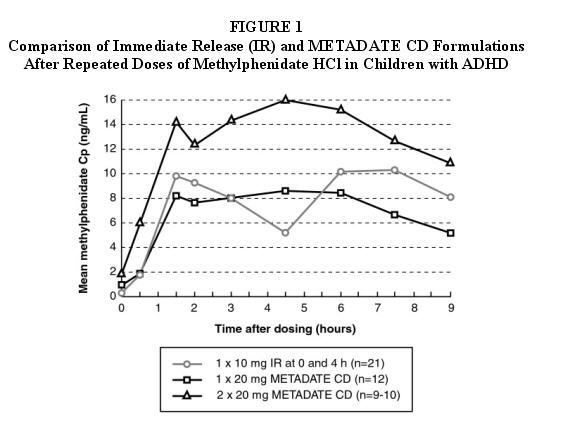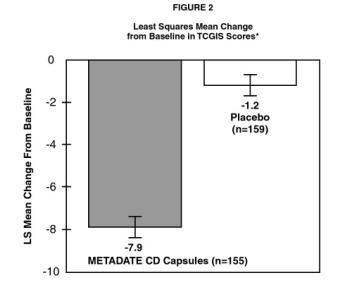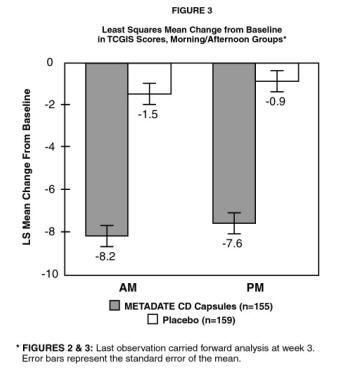 DRUG LABEL: Metadate CD
NDC: 54868-5397 | Form: CAPSULE, EXTENDED RELEASE
Manufacturer: Physicians Total Care, Inc.
Category: prescription | Type: HUMAN PRESCRIPTION DRUG LABEL
Date: 20101101
DEA Schedule: CII

ACTIVE INGREDIENTS: METHYLPHENIDATE HYDROCHLORIDE 10 mg/1 1
INACTIVE INGREDIENTS: POVIDONE; HYPROMELLOSES; POLYETHYLENE GLYCOL; ETHYLCELLULOSES; DIBUTYL SEBACATE; GELATIN; TITANIUM DIOXIDE; FD&C BLUE NO. 2; FERRIC OXIDE YELLOW

Metadate CD®
(methylphenidate HCl, USP)
Extended-Release Capsules
CII

Once Daily

DESCRIPTION

METADATE CD is a central nervous system (CNS) stimulant. The extended-release capsules comprise both immediate-release (IR) and extended-release (ER) beads such that 30% of the dose is provided by the IR component and 70% of the dose is provided by the ER component. METADATE CD is available in six capsule strengths containing 10 mg (3 mg IR; 7 mg ER), 20 mg (6 mg IR; 14 mg ER), 30 mg (9 mg IR; 21 mg ER), 40 mg (12 mg IR; 28 mg ER), 50 mg (15 mg IR; 35 mg ER), or 60 mg (18 mg IR; 42 mg ER) of methylphenidate hydrochloride for oral administration.

Chemically, methylphenidate HCl is d,l (racemic)-threo-methyl α-phenyl-2-piperidineacetate hydrochloride. Its empirical formula is C14H19NO2•HCl. Its structural formula is:

Methylphenidate HCl USP is a white, odorless, crystalline powder. Its solutions are acid to litmus. It is freely soluble in water and in methanol, soluble in alcohol, and slightly soluble in chloroform and in acetone. Its molecular weight is 269.77.

METADATE CD also contains the following inert ingredients: Sugar spheres, povidone, hydroxypropylmethylcellulose and polyethylene glycol, ethylcellulose aqueous dispersion, dibutyl sebacate, gelatin, and titanium dioxide.

The individual capsules contain the following color agents:

10 mg capsules: FD&C Blue No. 2, FDA/E172 Yellow Iron Oxide
20 mg capsules: FD&C Blue No. 2
30 mg capsules: FD&C Blue No. 2, FDA/E172 Red Iron Oxide
40 mg capsules: FDA/E172 Yellow Iron Oxide
50 mg capsules: FD&C Blue No. 2, FDA/E172 Red Iron Oxide

CLINICAL PHARMACOLOGY

Pharmacodynamics

Methylphenidate HCl is a central nervous system (CNS) stimulant. The mode of therapeutic action in Attention Deficit Hyperactivity Disorder (ADHD) is not known. Methylphenidate is thought to block the reuptake of norepinephrine and dopamine into the presynaptic neuron and increase the release of these monoamines into the extraneuronal space. Methylphenidate is a racemic mixture comprised of the d- and l-threo enantiomers. The d-threo enantiomer is more pharmacologically active than the l-threo enantiomer.

Pharmacokinetics

The pharmacokinetics of the METADATE CD methylphenidate hydrochloride formulation have been studied in healthy adult volunteers and in children with Attention Deficit Hyperactivity Disorder (ADHD).

Absorption And Distribution

Methylphenidate is readily absorbed. METADATE CD has a plasma/time concentration profile showing two phases of drug release with a sharp, initial slope similar to a methylphenidate immediate-release tablet, and a second rising portion approximately three hours later, followed by a gradual decline. (See Figure 1 below.)

Comparison Of Immediate Release (IR) And METADATE CD Formulations After Repeated Doses Of Methylphenidate HCl In Children With ADHD

METADATE CD was administered as repeated once-daily doses of 20 mg or 40 mg to children aged 7-12 years with ADHD for one week. After a dose of 20 mg, the mean (±SD) early Cmax was 8.6 (±2.2) ng/mL, the later Cmax was 10.9 (±3.9)* ng/mL and AUC0-9h was 63.0 (±16.8) ng•h/mL. The corresponding values after a 40 mg dose were 16.8 (±5.1) ng/mL, 15.1 (±5.8)* ng/mL and 120 (±39.6) ng•h/mL, respectively. The early peak concentrations (median) were reached about 1.5 hours after dose intake, and the second peak concentrations (median) were reached about 4.5 hours after dose intake. The means for Cmax and AUC following a dose of 20 mg were slightly lower than those seen with 10 mg of the immediate-release formulation, dosed at 0 and 4 hours.

*25-30% of the subjects had only one observed peak (Cmax) concentration of methylphenidate.

Dose Proportionality

Following single oral doses of 10-60 mg methylphenidate free base as a solution given to ten healthy male volunteers, Cmax and AUC increased proportionally with increasing doses. After the 60 mg dose, tmax was reached 1.5 hours post-dose, with a mean Cmax of 31.8 ng/mL (range 24.7-40.9 ng/mL).

Following one week of repeated once-daily doses of 20 mg or 40 mg METADATE CD to children aged 7-12 years with ADHD, Cmax and AUC were proportional to the administered dose.

Food Effects

In a study in adult volunteers to investigate the effects of a high-fat meal on the bioavailability of a dose of 40 mg, the presence of food delayed the early peak by approximately 1 hour (range -2 to 5 hours delay). The plasma levels rose rapidly following the food-induced delay in absorption. Overall, a high-fat meal increased the Cmax of METADATE CD by about 30% and AUC by about 17%, on average (see DOSAGE and ADMINISTRATION).

After a single dose, the bioavailability (Cmax and AUC) of methylphenidate in 26 healthy adults was unaffected by sprinkling the capsule contents on applesauce as compared to the intact capsule. This finding demonstrates that a 20 mg METADATE CD Capsule, when opened and sprinkled on one tablespoon of applesauce, is bioequivalent to the intact capsule.

Metabolism And Excretion

In humans, methylphenidate is metabolized primarily via deesterification to alpha-phenyl-piperidine acetic acid (ritalinic acid). The metabolite has little or no pharmacologic activity.

In vitro studies showed that methylphenidate was not metabolized by cytochrome P450 isoenzymes, and did not inhibit cytochrome P450 isoenzymes at clinically observed plasma drug concentrations.

The mean terminal half-life (t½) of methylphenidate following administration of METADATE CD (t½=6.8h) is longer than the mean terminal (t½) following administration of methylphenidate hydrochloride immediate-release tablets (t½=2.9h) and methylphenidate hydrochloride sustained-release tablets (t½=3.4h) in healthy adult volunteers. This suggests that the elimination process observed for METADATE CD is controlled by the release rate of methylphenidate from the extended-release formulation, and that the drug absorption is the rate-limiting process.

Special Populations

Gender

The pharmacokinetics of methylphenidate after a single dose of METADATE CD were similar between adult men and women.

Race

The influence of race on the pharmacokinetics of methylphenidate after METADATE CD administration has not been studied.

Age

The pharmacokinetics of methylphenidate after METADATE CD administration have not been studied in children less than 6 years of age.

Renal Insufficiency

There is no experience with the use of METADATE CD in patients with renal insufficiency. After oral administration of radiolabeled methylphenidate in humans, methylphenidate was extensively metabolized and approximately 80% of the radioactivity was excreted in the urine in the form of ritalinic acid. Since renal clearance is not an important route of methylphenidate clearance, renal insufficiency is expected to have little effect on the pharmacokinetics of METADATE CD.

Hepatic Insufficiency

There is no experience with the use of METADATE CD in patients with hepatic insufficiency.

CLINICAL STUDIES

METADATE CD was evaluated in a double-blind, parallel-group, placebo-controlled trial in which 321 untreated or previously treated pediatric patients with a DSM-IV diagnosis of Attention Deficit Hyperactivity Disorder (ADHD), 6 to 15 years of age, received a single morning dose for up to 3 weeks. Patients were required to have the combined or predominantly hyperactive-impulsive subtype of ADHD; patients with the predominantly inattentive subtype were excluded. Patients randomized to the METADATE CD group received 20 mg daily for the first week. Their dosage could be increased weekly to a maximum of 60 mg by the third week, depending on individual response to treatment.

The patient's regular school teacher completed the teachers' version of the Conners' Global Index Scale (TCGIS), a scale for assessing ADHD symptoms, in the morning and again in the afternoon on three alternate days of each treatment week. The change from baseline of the overall average (i.e., an average of morning and afternoon scores over 3 days) of the total TCGIS scores during the last week of treatment was analyzed as the primary efficacy parameter. Patients treated with METADATE CD showed a statistically significant improvement in symptom scores from baseline over patients who received placebo. (See Figure 2.) Separate analyses of TCGIS scores in the morning and afternoon revealed superiority in improvement with METADATE CD over placebo during both time periods. (See Figure 3.) This demonstrates that a single morning dose of METADATE CD exerts a treatment effect in both the morning and the afternoon.

INDICATION AND USAGE

Attention Deficit Hyperactivity Disorder (ADHD)

METADATE CD (methylphenidate HCl, USP) Extended-Release Capsules are indicated for the treatment of Attention Deficit Hyperactivity Disorder (ADHD).

The efficacy of METADATE CD in the treatment of ADHD was established in one controlled trial of children aged 6 to 15 who met DSM-IV criteria for ADHD (see CLINICAL PHARMACOLOGY).

A diagnosis of Attention Deficit Hyperactivity Disorder (ADHD; DSM-IV) implies the presence of hyperactive-impulsive or inattentive symptoms that caused impairment and were present before age 7 years. The symptoms must cause clinically significant impairment, e.g., in social, academic, or occupational functioning, and be present in two or more settings, e.g., school (or work) and at home. The symptoms must not be better accounted for by another mental disorder. For the Inattentive Type, at least six of the following symptoms must have persisted for at least 6 months: lack of attention to details/careless mistakes; lack of sustained attention; poor listener; failure to follow through on tasks; poor organization; avoids tasks requiring sustained mental effort; loses things; easily distracted; forgetful. For the Hyperactive-Impulsive Type, at least six of the following symptoms must have persisted for at least 6 months: fidgeting/squirming; leaving seat; inappropriate running/climbing; difficulty with quiet activities; "on the go;" excessive talking; blurting answers; can't wait turn; intrusive. The Combined Types requires both inattentive and hyperactive-impulsive criteria to be met.

Special Diagnostic Considerations

Specific etiology of this syndrome is unknown, and there is no single diagnostic test. Adequate diagnosis requires the use not only of medical but of special psychological, educational, and social resources. Learning may or may not be impaired. The diagnosis must be based upon a complete history and evaluation of the child and not solely on the presence of the required number of DSM-IV characteristics.

Need For Comprehensive Treatment Program

METADATE CD is indicated as an integral part of a total treatment program for ADHD that may include other measures (psychological, educational, social) for patients with this syndrome. Drug treatment may not be indicated for all children with this syndrome. Stimulants are not intended for use in the child who exhibits symptoms secondary to environmental factors and/or other primary psychiatric disorders, including psychosis. Appropriate educational placement is essential and psychosocial intervention is often helpful. When remedial measures alone are insufficient, the decision to prescribe stimulant medication will depend upon the physician's assessment of the chronicity and severity of the child's symptoms.

Long-Term Use

The effectiveness of METADATE CD for long-term use, i.e., for more than 3 weeks, has not been systematically evaluated in controlled trials. Therefore, the physician who elects to use METADATE CD for extended periods should periodically re-evaluate the long-term usefulness of the drug for the individual patient (see DOSAGE and ADMINISTRATION).

CONTRAINDICATIONS

Agitation

METADATE CD is contraindicated in patients with marked anxiety, tension and agitation, since the drug may aggravate these symptoms.

Hypersensitivity To Methylphenidate Or Other Excipients

METADATE CD is contraindicated in patients known to be hypersensitive to methylphenidate or other components of the product.

METADATE CD contains sucrose. Therefore, patients with rare hereditary problems of fructose intolerance, glucose-galactose malabsorption, or sucrase-isomaltase insufficiency should not take this medicine.

Glaucoma

METADATE CD is contraindicated in patients with glaucoma.

Tics

METADATE CD is contraindicated in patients with motor tics or with a family history or diagnosis of Tourette's syndrome (see ADVERSE REACTIONS).

Monoamine Oxidase Inhibitors

METADATE CD is contraindicated during treatment with monoamine oxidase inhibitors, and also within a minimum of 14 days following discontinuation of a monoamine oxidase inhibitor (hypertensive crises may result).

Hypertension And Other Cardiovascular Conditions

METADATE CD is contraindicated in patients with severe hypertension, angina pectoris, cardiac arrhythmias, heart failure, recent myocardial infarction, hyperthyroidism or thyrotoxicosis (see WARNINGS).

Halogenated Anesthetics

There is a risk of sudden blood pressure increase during surgery. If surgery is planned, METADATE CD should not be taken on the day of the surgery.

WARNINGS

Serious Cardiovascular Events

Sudden Death And Pre-existing Structural Cardiac Abnormalities Or Other Serious Heart Problems

Children And Adolescents

Sudden death has been reported in association with CNS stimulant treatment at usual doses in children and adolescents with structural cardiac abnormalities or other serious heart problems. Although some serious heart problems alone carry an increased risk of sudden death, stimulant products generally should not be used in children or adolescents with known serious structural cardiac abnormalities, cardiomyopathy, serious heart rhythm abnormalities, or other serious cardiac problems that may place them at increased vulnerability to the sympathomimetic effects of a stimulant drug (see CONTRAINDICATIONS).

Adults

Sudden deaths, stroke, and myocardial infarction have been reported in adults taking stimulant drugs at usual doses for ADHD. Although the role of stimulants in these adult cases is also unknown, adults have a greater likelihood than children of having serious structural cardiac abnormalities, cardiomyopathy, serious heart rhythm abnormalities, coronary artery disease, or other serious cardiac problems. Adults with such abnormalities should also generally not be treated with stimulant drugs (see CONTRAINDICATIONS).

Hypertension And Other Cardiovascular Conditions

Stimulant medications cause a modest increase in average blood pressure (about 2-4 mmHg) and average heart rate (about 3-6 bpm), and individuals may have larger increases. While the mean changes alone would not be expected to have short-term consequences, all patients should be monitored for larger changes in heart rate and blood pressure. Caution is indicated in treating patients whose underlying medical conditions might be compromised by increases in blood pressure or heart rate, e.g., those with pre-existing hypertension, heart failure, recent myocardial infarction, or ventricular arrhythmia (see CONTRAINDICATIONS).

Assessing Cardiovascular Status In Patients Being Treated With Stimulant Medications

Children, adolescents, or adults who are being considered for treatment with stimulant medications should have a careful history (including assessment for a family history of sudden death or ventricular arrhythmia) and physical exam to assess for the presence of cardiac disease, and should receive further cardiac evaluation if findings suggest such disease (e.g., electrocardiogram and echocardiogram). Patients who develop symptoms such as exertional chest pain, unexplained syncope, or other symptoms suggestive of cardiac disease during stimulant treatment should undergo a prompt cardiac evaluation.

Psychiatric Adverse Events

Pre-Existing Psychosis

Administration of stimulants may exacerbate symptoms of behavior disturbance and thought disorder in patients with a pre-existing psychotic disorder.

Bipolar Illness

Particular care should be taken in using stimulants to treat ADHD in patients with comorbid bipolar disorder because of concern for possible induction of a mixed/manic episode in such patients. Prior to initiating treatment with a stimulant, patients with comorbid depressive symptoms should be adequately screened to determine if they are at risk for bipolar disorder; such screening should include a detailed psychiatric history, including a family history of suicide, bipolar disorder, and depression.

Emergence Of New Psychotic Or Manic Symptoms

Treatment emergent psychotic or manic symptoms, e.g., hallucinations, delusional thinking, or mania in children and adolescents without prior history of psychotic illness or mania can be caused by stimulants at usual doses. If such symptoms occur, consideration should be given to a possible causal role of the stimulant, and discontinuation of treatment may be appropriate. In a pooled analysis of multiple short-term, placebo-controlled studies, such symptoms occurred in about 0.1% (4 patients with events out of 3482 exposed to methylphenidate or amphetamine for several weeks at usual doses) of stimulant-treated patients compared to 0 in placebo-treated patients.

Aggression

Aggressive behavior or hostility is often observed in children and adolescents with ADHD, and has been reported in clinical trials and the postmarketing experience of some medications indicated for the treatment of ADHD. Although there is no systematic evidence that stimulants cause aggressive behavior or hostility, patients beginning treatment for ADHD should be monitored for the appearance of or worsening of aggressive behavior or hostility.

Long-Term Suppression Of Growth

Careful follow-up of weight and height in children ages 7 to 10 years who were randomized to either methylphenidate or non-medication treatment groups over 14 months, as well as in naturalistic subgroups of newly methylphenidate-treated and non-medication treated children over 36 months (to the ages of 10 to 13 years), suggests that consistently medicated children (i.e., treatment for 7 days per week throughout the year) have a temporary slowing in growth rate (on average, a total of about 2 cm less growth in height and 2.7 kg less growth in weight over 3 years), without evidence of growth rebound during this period of development. Published data are inadequate to determine whether chronic use of amphetamines may cause a similar suppression of growth, however, it is anticipated that they likely have this effect as well. Therefore, growth should be monitored during treatment with stimulants, and patients who are not growing or gaining height or weight as expected may need to have their treatment interrupted.

Seizures

There is some clinical evidence that stimulants may lower the convulsive threshold in patients with prior history of seizures, in patients with prior EEG abnormalities in absence of seizures, and, very rarely, in patients without a history of seizures and no prior EEG evidence of seizures. In the presence of seizures, the drug should be discontinued.

Visual Disturbance

Difficulties with accommodation and blurring of vision have been reported with stimulant treatment.

Use In Children Under Six Years Of Age

METADATE CD should not be used in children under six years, since safety and efficacy in this age group have not been established.

Drug Dependence

METADATE CD should be given cautiously to patients with a history of drug dependence or alcoholism. Chronic abusive use can lead to marked tolerance and psychological dependence with varying degrees of abnormal behavior. Frank psychotic episodes can occur, especially with parenteral abuse. Careful supervision is required during withdrawal from abusive use since severe depression may occur. Withdrawal following chronic therapeutic use may unmask symptoms of the underlying disorder that may require follow-up.

PRECAUTIONS

Hematologic Monitoring

Periodic CBC, differential, and platelet counts are advised during prolonged therapy.

Drug Testing

METADATE CD contains methylphenidate which may result in a positive result during drug testing.

Information For Patients

Patients should be instructed to take one dose in the morning before breakfast. The patients should be instructed that the capsule may be swallowed whole, or alternatively, the capsule may be opened and the capsule contents sprinkled onto a small amount (tablespoon) of applesauce and given immediately, and not stored for future use. The capsules and the capsule contents must not be crushed or chewed.

Prescribers or other health professionals should inform patients, their families, and their caregivers about the benefits and risks associated with treatment with methylphenidate and should counsel them in its appropriate use. A patient Medication Guide is available for METADATE CD. The prescriber or healthcare professional should instruct patients, their families, and their caregivers to read the Medication Guide and should assist them in understanding its contents. Patients should be given the opportunity to discuss the contents of the Medication Guide and to obtain answers to any questions they may have. The complete text of the Medication Guide is reprinted at the end of this document. The Medication Guide may also be found in the full prescribing information for METADATE CD on http://ucb-group.com/products/cns/equasym-metadate/ or by calling 1-866-822-0068.

Drug Interactions

Because of possible effects on blood pressure, METADATE CD should be used cautiously with pressor agents.

Human pharmacologic studies have shown that methylphenidate may inhibit the metabolism of coumarin anticoagulants, anticonvulsants (e.g., phenobarbital, phenytoin, primidone), phenylbutazone and some antidepressants (tricyclics and selective serotonin reuptake inhibitors). Downward dose adjustment of these drugs may be required when given concomitantly with methylphenidate. It may be necessary to adjust the dosage and monitor plasma drug concentrations (or, in the case of coumarin, coagulation times), when initiating or discontinuing concomitant methylphenidate.

In theory, there is a possibility that the clearance of methylphenidate might be affected by urinary pH, either being increased with acidifying agents or decreased with alkalizing agents. This should be considered when methylphenidate is given in combination with agents that alter urinary pH.

Halogenated Anesthetics

There is a risk of sudden blood pressure increase during surgery. If surgery is planned, METADATE CD should not be taken the day of the surgery.

Carcinogenesis, Mutagenesis, And Impairment Of Fertility

In a lifetime carcinogenicity study carried out in B6C3F1 mice, methylphenidate caused an increase in hepatocellular adenomas and, in males only, an increase in hepatoblastomas, at a daily dose of approximately 60 mg/kg/day. This dose is approximately 30 times and 4 times the maximum recommended human dose of METADATE CD on a mg/kg and mg/m^2 basis, respectively. Hepatoblastoma is a relatively rare rodent malignant tumor type. There was no increase in total malignant hepatic tumors. The mouse strain used is sensitive to the development of hepatic tumors, and the significance of these results to humans is unknown.

Methylphenidate did not cause any increases in tumors in a lifetime carcinogenicity study carried out in F344 rats; the highest dose used was approximately 45 mg/kg/day, which is approximately 22 times and 5 times the maximum recommended human dose of METADATE CD on a mg/kg and mg/m^2 basis, respectively.

In a 24-week carcinogenicity study in the transgenic mouse strain p53+/-, which is sensitive to genotoxic carcinogens, there was no evidence of carcinogenicity. Male and female mice were fed diets containing the same concentration of methylphenidate as in the lifetime carcinogenicity study; the high-dose groups were exposed to 60 to 74 mg/kg/day of methylphenidate.

Methylphenidate was not mutagenic in the in vitro Ames reverse mutation assay or in the in vitro mouse lymphoma cell forward mutation assay. Sister chromatid exchanges and chromosome aberrations were increased, indicative of a weak clastogenic response, in an in vitro assay in cultured Chinese Hamster Ovary cells. Methylphenidate was negative in vivo in males and females in the mouse bone marrow micronucleus assay.

Methylphenidate did not impair fertility in male or female mice that were fed diets containing the drug in an 18-week Continuous Breeding study. The study was conducted at doses up to 160 mg/kg/day, approximately 80-fold and 8-fold the highest recommended human dose of METADATE CD on a mg/kg and mg/m^2 basis, respectively.

Pregnancy

Teratogenic Effects

Pregnancy Category C

Methylphenidate has been shown to have teratogenic effects in rabbits when given in doses of 200 mg/kg/day, which is approximately 100 times and 40 times the maximum recommended human dose on a mg/kg and mg/m^2 basis, respectively.

A reproduction study in rats revealed no evidence of teratogenicity at an oral dose of 58 mg/kg/day. However, this dose, which caused some maternal toxicity, resulted in decreased postnatal pup weights and survival when given to the dams from day one of gestation through the lactation period. This dose is approximately 30 fold and 6 fold the maximum recommended human dose of METADATE CD on a mg/kg and mg/m^2 basis, respectively.

There are no adequate and well-controlled studies in pregnant women. METADATE CD should be used during pregnancy only if the potential benefit justifies the potential risk to the fetus.

Nursing Mothers

It is not known whether methylphenidate is excreted in human milk. Because many drugs are excreted in human milk, caution should be exercised if METADATE CD is administered to a nursing woman.

Pediatric Use

The safety and efficacy of METADATE CD in children under 6 years old have not been established. Long-term effects of methylphenidate in children have not been well established (see WARNINGS).

ADVERSE REACTIONS

The premarketing development program for METADATE CD included exposures in a total of 228 participants in clinical trials (188 pediatric patients with ADHD, 40 healthy adult subjects). These participants received METADATE CD 20, 40, and/or 60 mg/day. The 188 patients (ages 6 to 15) were evaluated in one controlled clinical study, one controlled, crossover clinical study, and one uncontrolled clinical study. Safety data on all patients are included in the discussion that follows. Adverse reactions were assessed by collecting adverse events, results of physical examinations, vital signs, weights, laboratory analyses, and ECGs.

Adverse events during exposure were obtained primarily by general inquiry and recorded by clinical investigators using terminology of their own choosing. Consequently, it is not possible to provide a meaningful estimate of the proportion of individuals experiencing adverse events without first grouping similar types of events into a smaller number of standardized event categories. In the tables and listings that follow, COSTART terminology has been used to classify reported adverse events.

The stated frequencies of adverse events represent the proportion of individuals who experienced, at least once, a treatment-emergent adverse event of the type listed. An event was considered treatment emergent if it occurred for the first time or worsened while receiving therapy following baseline evaluation.

Adverse Findings In Clinical Trials With METADATE CD

Adverse Events Associated With Discontinuation Of Treatment

In the 3-week placebo-controlled, parallel-group trial, two METADATE CD-treated patients (1%) and no placebo-treated patients discontinued due to an adverse event (rash and pruritus; and headache, abdominal pain, and dizziness, respectively).

Adverse Events Occurring At An Incidence Of 5% Or More Among METADATE CD-Treated Patients

Table 1 enumerates, for a pool of the three studies in pediatric patients with ADHD, at METADATE CD doses of 20, 40, or 60 mg/day, the incidence of treatment-emergent adverse events. One study was a 3-week placebo-controlled, parallel-group trial, one study was a controlled, crossover trial, and the third study was an open titration trial. The table includes only those events that occurred in 5% or more of patients treated with METADATE CD where the incidence in patients treated with METADATE CD was greater than the incidence in placebo-treated patients.

The prescriber should be aware that these figures cannot be used to predict the incidence of adverse events in the course of usual medical practice where patient characteristics and other factors differ from those which prevailed in the clinical trials. Similarly, the cited frequencies cannot be compared with figures obtained from other clinical investigations involving different treatments, uses, and investigators. The cited figures, however, do provide the prescribing physician with some basis for estimating the relative contribution of drug and non-drug factors to the adverse event incidence rate in the population studied.

TABLE 1 Incidence of Treatment-Emergent Events^1 in a Pool of 3-4 Week Clinical Trials of METADATE CD
Body System | Preferred Term | METADATE CD (n=188) | Placebo (n=190)
General | Headache | 12% | 8%
 | Abdominal pain (stomach ache) | 7% | 4%
Digestive System | Anorexia (loss of appetite) | 9% | 2%
Nervous System | Insomnia | 5% | 2%
^1: Events, regardless of causality, for which the incidence for patients treated with METADATE CD was at least 5% and greater than the incidence among placebo-treated patients. Incidence has been rounded to the nearest whole number.

Adverse Events With Other Marketed Methylphenidate HCl Products

Nervousness and insomnia are the most common adverse reactions reported with other methylphenidate products. Other reactions include hypersensitivity (including skin rash, urticaria, fever, arthralgia, exfoliative dermatitis, erythema multiforme with histopathological findings of necrotizing vasculitis, and thrombocytopenic purpura); anorexia; nausea; dizziness; palpitations; headache; dyskinesia; drowsiness; blood pressure and pulse changes, both up and down; tachycardia; angina; cardiac arrhythmia; abdominal pain; weight loss during prolonged therapy. There have been rare reports of Tourette's Syndrome and obsessive-compulsive disorder. Toxic psychosis has been reported. Although a definite causal relationship has not been established, the following have been reported in patients taking this drug: instances of abnormal liver function, ranging from transaminase elevation to hepatic coma; isolated cases of cerebral arteritis and/or occlusion; leucopenia and/or anemia; transient depressed mood; a few instances of scalp hair loss. Very rare reports of neuroleptic malignant syndrome (NMS) have been reported, and, in most of these, patients were concurrently receiving therapies associated with NMS. In a single report, a ten year old boy who had been taking methylphenidate for approximately 18 months experienced an NMS-like event within 45 minutes of ingesting his first dose of venlafaxine. It is uncertain whether this case represented a drug-drug interaction, a response to either drug alone, or some other cause.

In children, loss of appetite, abdominal pain, weight loss during prolonged therapy, insomnia and tachycardia may occur more frequently; however, any of the other adverse reactions listed above may also occur.

Postmarketing Experience

In addition to the adverse events listed above, the following have been reported in patients receiving METADATE CD worldwide. The list is alphabetized: abnormal behavior, aggression, anxiety, cardiac arrest, depression, fixed drug eruption, hyperactivity, irritability, migraine, obsessive-compulsive disorder, peripheral coldness, Raynaud's phenomenon, reversible ischaemic neurological deficit, sudden death, suicidal behavior (including completed suicide), and thrombocytopenia. Data are insufficient to support an estimation of incidence or establish causation.

DRUG ABUSE AND DEPENDENCE

Controlled Substance Class

METADATE CD, like other methylphenidate products, is classified as a Schedule II controlled substance by federal regulation.

Abuse, Dependence, And Tolerance

See WARNINGS for boxed warning containing drug abuse and dependence information.

OVERDOSAGE

Signs and symptoms of acute methylphenidate overdosage, resulting principally from overstimulation of the CNS and from excessive sympathomimetic effects, may include the following: vomiting, agitation, tremors, hyperreflexia, muscle twitching, convulsions (may be followed by coma), euphoria, confusion, hallucinations, delirium, sweating, flushing, headache, hyperpyrexia, tachycardia, palpitations, cardiac arrhythmias, hypertension, mydriasis, and dryness of mucous membranes.

Recommended Treatment

Treatment consists of appropriate supportive measures. The patient must be protected against self-injury and against external stimuli that would aggravate overstimulation already present. Gastric contents may be evacuated by gastric lavage as indicated. Before performing gastric lavage, control agitation and seizures if present and protect the airway. Other measures to detoxify the gut include administration of activated charcoal and a cathartic. Intensive care must be provided to maintain adequate circulation and respiratory exchange; external cooling procedures may be required for hyperpyrexia.

Efficacy of peritoneal dialysis or extracorporeal hemodialysis for METADATE CD overdosage has not been established.

The prolonged release of methylphenidate from METADATE CD should be considered when treating patients with overdose.

Poison Control Center

As with the management of all overdosage, the possibility of multiple drug ingestion should be considered. The physician may wish to consider contacting a poison control center for up-to-date information on the management of overdosage with methylphenidate.

DOSAGE AND ADMINISTRATION

METADATE CD is administered once daily in the morning, before breakfast.

METADATE CD may be swallowed whole with the aid of liquids, or alternatively, the capsule may be opened and the capsule contents sprinkled onto a small amount (tablespoon) of applesauce and given immediately, and not stored for future use. Drinking some fluids, e.g. water, should follow the intake of the sprinkles with applesauce. The capsules and the capsule contents must not be crushed or chewed (see PRECAUTIONS: Information for Patients).

Dosage should be individualized according to the needs and responses of the patient.

Initial Treatment

The recommended starting dose of METADATE CD is 20 mg once daily. Dosage may be adjusted in weekly 10-20 mg increments to a maximum of 60 mg/day taken once daily in the morning, depending upon tolerability and degree of efficacy observed. Daily dosage above 60 mg is not recommended.

Maintenance/Extended Treatment

There is no body of evidence available from controlled trials to indicate how long the patient with ADHD should be treated with METADATE CD. It is generally agreed, however, that pharmacological treatment of ADHD may be needed for extended periods. Nevertheless, the physician who elects to use METADATE CD for extended periods in patients with ADHD should periodically re-evaluate the long-term usefulness of the drug for the individual patient with trials off medication to assess the patient's functioning without pharmacotherapy. Improvement may be sustained when the drug is either temporarily or permanently discontinued.

Dose Reduction And Discontinuation

If paradoxical aggravation of symptoms or other adverse events occur, the dosage should be reduced, or, if necessary, the drug should be discontinued.

If improvement is not observed after appropriate dosage adjustment over a one-month period, the drug should be discontinued.

HOW SUPPLIED

METADATE CD (methylphenidate HCl, USP) Extended-Release Capsules are available in six strengths:

10 mg, green/white capsules, imprinted with "UCB 579" in white letters on the green cap, and "10 mg" in black letters on the white body of the capsule.

Bottles of 10 | NDC 54868-5397-1
Bottles of 30 | NDC 54868-5397-0

20 mg, blue/white capsules, imprinted with "UCB 580" in white letters on the blue cap, and "20 mg" in black letters on the white body of the capsule.

Bottles of 10 | NDC 54868-4718-1
Bottles of 30 | NDC 54868-4718-0

30 mg, reddish-brown/white capsules, imprinted with "UCB 581" in white letters on the reddish-brown cap, and "30 mg" in black letters on the white body of the capsule.

Bottles of 10 | NDC 54868-0668-1
Bottles of 30 | NDC 54868-0668-0

50 mg, purple/white capsules, imprinted with "UCB 583" in white letters on the purple cap, and "50 mg" in black letters on the white body of the capsule.

Bottles of 10 | NDC 54868-6234-1
Bottles of 30 | NDC 54868-6234-0

STORAGE AND HANDLING

Store at 25°C (77°F); excursions permitted to 15°-30°C (59°-86°F) [See USP Controlled Room Temperature].

Keep out of the reach of children.

REFERENCE

American Psychiatric Association. Diagnostic and Statistical Manual of Mental Disorders. American Psychiatric Association 1994. 4th ed. Washington D.C.

For Medical Information
Contact: Medical Affairs Department
Phone: (866) 822-0068
Fax: (770) 970-8859

Marketed by UCB, Inc.
Smyrna, GA 30080

Manufactured by UCB Manufacturing, Inc.
Rochester, NY 14623

9E 09/2010

METADATE CD is a registered trademark of the UCB Group of companies

©2010, UCB, Inc., Smyrna, GA 30080
All rights reserved. Printed in U.S.A.

Relabeling and Repackaging by:
Physicians Total Care, Inc.
Tulsa, OK 74146

MEDICATION GUIDE

METADATE CD®
(methylphenidate HCl, USP) Extended-Release Capsules CII

Read the Medication Guide that comes with METADATE CD before you or your child starts taking it and each time you get a refill. There may be new information. This Medication Guide does not take the place of talking to your doctor about your or your child's treatment with METADATE CD.

What is the most important information I should know about Metadate CD?
The following have been reported with use of methylphenidate HCl, USP and other stimulant medicines.
1. Heart-related problems:

- sudden death in patients who have heart problems or heart defects
- stroke and heart attack in adults
- increased blood pressure and heart rate

Tell your doctor if you or your child have any heart problems, heart defects, high blood pressure, or a family history of these problems.

Your doctor should check you or your child carefully for heart problems before starting METADATE CD.

Your doctor should check your or your child's blood pressure and heart rate regularly during treatment with METADATE CD.

Call your doctor right away if you or your child has any signs of heart problems such as chest pain, shortness of breath, or fainting while taking METADATE CD.
2. Mental (Psychiatric) problems:
All Patients

- new or worse behavior and thought problems
- new or worse bipolar illness
- new or worse aggressive behavior or hostility

Children and Teenagers

- new psychotic symptoms (such as hearing voices, believing things that are not true, are suspicious) or new manic symptoms

Tell your doctor about any mental problems you or your child have, or about a family history of suicide, bipolar illness, or depression.

Call your doctor right away if you or your child have any new or worsening mental symptoms or problems while taking METADATE CD, especially seeing or hearing things that are not real, believing things that are not real, or are suspicious.

What Is METADATE CD?

METADATE CD is a central nervous system stimulant prescription medicine. It is used for the treatment of Attention-Deficit Hyperactivity Disorder (ADHD).

METADATE CD may help increase attention and decrease impulsiveness and hyperactivity in patients with ADHD.

METADATE CD should be used as a part of a total treatment program for ADHD that may include counseling or other therapies.

BOXED WARNING

METADATE CD is a federally controlled substance (CII) because it can be abused or lead to dependence. Keep METADATE CD in a safe place to prevent misuse and abuse. Selling or giving away METADATE CD may harm others, and is against the law.
Tell your doctor if you or your child have (or have a family history of) ever abused or been dependent on alcohol, prescription medicines or street drugs.

Who should not take METADATE CD?

METADATE CD should not be taken if you or your child:

- are very anxious, tense, or agitated
- have an eye problem called glaucoma
- have tics or Tourette's syndrome, or a family history of Tourette's syndrome. Tics are hard to control repeated movements or sounds.
- have severe high blood pressure or a heart problem
- have hyperthyroidism
- are taking or have taken within the past 14 days an antidepression medicine called a monoamine oxidase inhibitor or MAOI.
- are allergic to anything in METADATE CD. See the end of this Medication Guide for a complete list of ingredients.

METADATE CD should not be used in children less than 6 years old because it has not been studied in this age group.

METADATE CD may not be right for you or your child. Before starting METADATE CD tell your or your child's doctor about all health conditions (or a family history of) including:

- heart problems, heart defects, high blood pressure
- mental problems including psychosis, mania, bipolar illness, or depression
- tics or Tourette's syndrome
- seizures or have had an abnormal brain wave test (EEG)

Tell your doctor if you or your child is pregnant, planning to become pregnant, or breastfeeding.

Can METADATE CD be taken with other medicines?

Tell your doctor about all of the medicines that you or your child take including prescription and nonprescription medicines, vitamins, and herbal supplements. METADATE CD and some medicines may interact with each other and cause serious side effects. Sometimes the doses of other medicines will need to be adjusted while taking METADATE CD.

Your doctor will decide whether METADATE CD can be taken with other medicines.

Especially tell your doctor if you or your child takes:

- anti-depression medicines including MAOIs
- seizure medicines
- blood thinner medicines
- blood pressure medicines
- cold or allergy medicines that contain decongestants

Know the medicines that you or your child takes. Keep a list of your medicines with you to show your doctor and pharmacist.

Do not start any new medicine while taking METADATE CD without talking to your doctor first.

How should METADATE CD be taken?

- Take METADATE CD exactly as prescribed. Your doctor may adjust the dose until it is right for you or your child.
- Take METADATE CD once each day in the morning before breakfast. METADATE CD is an extended release capsule. It releases medicine into your body throughout the day.
- METADATE CD can be taken with or without food.
- Swallow METADATE CD capsules whole with water or other liquids. If you cannot swallow the capsule, open it and sprinkle the medicine over a spoonful of applesauce. Swallow the applesauce and medicine mixture without chewing. Follow with a drink of water or other liquid. Never chew or crush the capsule or the medicine inside the capsule.
- From time to time, your doctor may stop METADATE CD treatment for a while to check ADHD symptoms.
- Your doctor may do regular checks of the blood, heart, and blood pressure while taking METADATE CD. Children should have their height and weight checked often while taking METADATE CD. METADATE CD treatment may be stopped if a problem is found during these check-ups.
- If you or your child takes too much METADATE CD or overdoses, call your doctor or poison control center right away, or get emergency treatment.

What are possible side effects of METADATE CD?

See "What is the most important information I should know about METADATE CD?" for information on reported heart and mental problems.

Other serious side effects include:

- slowing of growth (height and weight) in children
- seizures, mainly in patients with a history of seizures
- eyesight changes or blurred vision

Common side effects include:

- headache
- decreased appetite
- stomach ache
- nervousness
- trouble sleeping
- dizziness

Talk to your doctor if you or your child has side effects that are bothersome or do not go away.

This is not a complete list of possible side effects. Ask your doctor or pharmacist for more information

Call your doctor for medical advice about side effects. You may report side effects to FDA at 1-800-FDA-1088.

How should I store METADATE CD?

- Store METADATE CD in a safe place at room temperature, 59 to 86°F (15 to 30°C). Protect from moisture.
- Keep METADATE CD and all medicines out of the reach of children.

General information about METADATE CD

Medicines are sometimes prescribed for purposes other than those listed in a Medication Guide. Do not use METADATE CD for a condition for which it was not prescribed. Do not give METADATE CD to other people, even if they have the same condition. It may harm them and it is against the law.

This Medication Guide summarizes the most important information about METADATE CD. If you would like more information, talk with your doctor. You can ask your doctor or pharmacist for information about METADATE CD that was written for healthcare professionals. For more information about METADATE CD call 1-866-822-0068.

What are the ingredients in METADATE CD?

Active Ingredient: methylphenidate HCl
Inactive Ingredients: sugar spheres, povidone, hydroxypropylmethylcellulose and polyethylene glycol, ethylcellulose aqueous dispersion, dibutyl sebacate, gelatin, and titanium dioxide.

The individual capsules contain the following coloring agents:
10 mg capsules: FD&C Blue No. 2, FDA/E172 Yellow Iron Oxide
20 mg capsules: FD&C Blue No. 2
30 mg capsules: FD&C Blue No. 2, FDA/E172 Red Iron Oxide
40 mg capsules: FDA/E172 Yellow Iron Oxide
50 mg capsules: FD&C Blue No. 2, FDA/E172 Red Iron Oxide

This Medication Guide has been approved by the U.S. Food and Drug Administration.

Marketed by UCB, Inc.
Smyrna, GA 30080
Manufactured by UCB Manufacturing, Inc.
Rochester, NY 14623
METADATE CD is a registered trademark of the UCB Group of companies
©2009, UCB, Inc., Smyrna, GA 30080
All rights reserved. Printed in U.S.A.
2E 06/2009

PRINCIPAL DISPLAY PANEL - 10 mg Capsule Label

Once Daily

Metadate CD®
(methylphenidate HCl, USP)
Extended-Release Capsules
CII

10 mg

A Medication Guide is required
for every prescription dispensed.

Please use accompanying Medication Guide.

Rx Only

PRINCIPAL DISPLAY PANEL - 20 mg Capsule Label

Once Daily

Metadate CD®
(methylphenidate HCl, USP)
Extended-Release Capsules
CII

20 mg

A Medication Guide is required
for every prescription dispensed.

Please use accompanying Medication Guide.

Rx Only

PRINCIPAL DISPLAY PANEL - 30 mg Capsule Label

Once Daily

Metadate CD®
(methylphenidate HCl, USP)
Extended-Release Capsules
CII

30 mg

Rx Only

A Medication Guide is required
for every prescription dispensed.

Please use accompanying Medication Guide.

PRINCIPAL DISPLAY PANEL - 50 mg Capsule Label

Once Daily

Metadate CD®
(methylphenidate HCl, USP)
Extended-Release Capsules
CII

50 mg

Rx Only

A Medication Guide is required
for every prescription dispensed.

Please use accompanying Medication Guide.